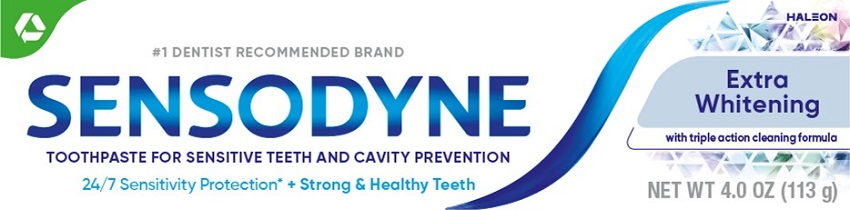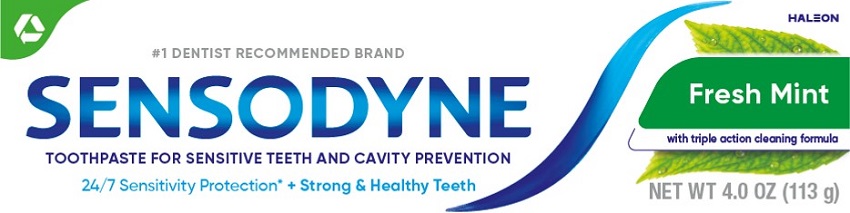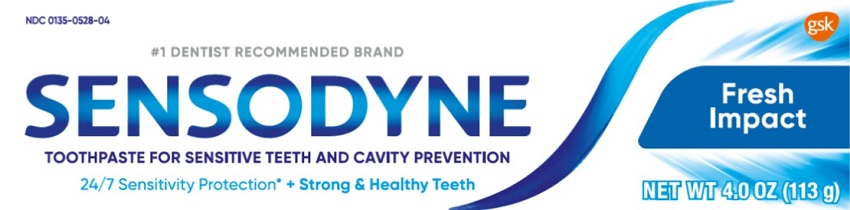 DRUG LABEL: Sensodyne
NDC: 0135-0525 | Form: PASTE
Manufacturer: Haleon US Holdings LLC
Category: otc | Type: HUMAN OTC DRUG LABEL
Date: 20240515

ACTIVE INGREDIENTS: POTASSIUM NITRATE 50 mg/1 g; SODIUM FLUORIDE 1.11 mg/1 g
INACTIVE INGREDIENTS: WATER; HYDRATED SILICA; SORBITOL; GLYCERIN; SODIUM TRIPOLYPHOSPHATE, UNSPECIFIED FORM; POLYETHYLENE GLYCOL 400; TITANIUM DIOXIDE; COCAMIDOPROPYL BETAINE; SODIUM METHYL COCOYL TAURATE; XANTHAN GUM; SODIUM HYDROXIDE; SACCHARIN SODIUM; SUCRALOSE

Drug Facts

Active ingredients

Potassium nitrate (5%)

Sensodyne Fresh Mint and Fresh Impact: Sodium fluoride 0.25% (0.15% w/v fluoride ion)

Sensodyne Extra Whitening: Sodium fluoride 0.24% (0.15% w/v fluoride ion)

Purposes

Antihypersensitivity

Anticavity

Uses

- builds increasing protection against painful sensitivity of the teeth to cold, heat, acids, sweets, or contact.
- aids in the prevention of dental cavities.

Warnings

Stop use and ask a dentist if

- the problem persists or worsens. Sensitive teeth may indicate a serious problem that may need prompt care by a dentist.
- pain/sensitivity still persists after 4 weeks of use.

Keep out of reach of children.

If more than used for brushing is accidentally swallowed, get medical help or contact a Poison Control Center right away.

Directions

- adults and children 12 years of age and older:
  - apply at least a 1-inch strip of the product onto a soft bristle toothbrush.
  - brush teeth thoroughly for at least 1 minute twice a day (morning and evening), and not more than 3 times a day, or as recommended by a dentist or doctor. Make sure to brush all sensitive areas of the teeth. Minimize swallowing. Spit out after brushing.
- children under 12 years of age:Consult a dentist or doctor.

Other information

- do not store above 30°C (86°F)

Inactive ingredients (Extra Whitening)

water, hydrated silica, sorbitol, glycerin, pentasodium triphosphate, PEG-8, flavor, titanium dioxide, cocamidopropyl betaine, sodium methyl cocoyl taurate, xanthan gum, sodium hydroxide, sodium saccharin, sucralose

Inactive ingredients (Fresh Mint)

water, sorbitol, hydrated silica, glycerin, flavor, cocamidopropyl betaine, xanthan gum, titanium dioxide, sodium saccharin, sodium hydroxide, sucralose, yellow 10, blue 1

Inactive ingredients (Fresh Impact)

water, sorbitol, hydrated silica, glycerin, cocamidopropyl betaine, flavor, xanthan gum, titanium dioxide, sodium saccharin, sodium hydroxide, sucralose, blue 1

Questions or comments?

1-866-844-2797

Additional Information

ALWAYS FOLLOW THE LABEL

Trademarks are owned by or licensed to the Haleon group of companies.

©2023 Haleon group of companies or its licensor.

Distributed by: Haleon, Warren, NJ 07059

Pat. Info www.productpats.com

Principal Display Panel

#1 DENTIST RECOMMENDED BRAND HALEON

SENSODYNE

Extra Whitening

with triple action cleaning formula

TOOTHPASTE FOR SENSITIVE TEETH AND CAVITY PREVENTION

24/7 SENSITIVITY PROTECTION* +Strong & Healthy Teeth

What are sensitive teeth?

Lots of people have sensitive teeth. When enamel is worn away (through eating everyday acidic food or drinks) or gums recede, the dentin underneath becomes exposed. This can lead to tooth sensitivity, for example, with cold and hot food and drinks.

What does Sensodyne do?

Sensodyne provides daily care for sensitive teeth* plus all the benefits you would expect from a daily

fluoride toothpaste - strong teeth and freshness.
*with twice daily brushing.

24/7 SENSITIVITY PROTECTION* + Strong & Healthy Teeth

Use Sensodyne Extra Whitening twice daily:

• Long lasting sensitivity protection• every day

• Contains fluoride to protect against cavities

NET WT 4.0 OZ (113g)

62000000208004 Front Carton

Principal Display Panel

#1 Dentist Recommended Brand HALEON

SENSODYNE

Fresh Mint

with triple action cleaning formula

TOOTHPASTE FOR SENSITIVE TEETH AND CAVITY PREVENTION

24/7 SENSITIVITY PROTECTION* +Strong & Healthy Teeth

NET WT 4.0 OZ (113 g)

What are sensitive teeth?

Lots of people have sensitive teeth. When enamel is worn away (through eating everyday acidic food or drinks) or gums recede, the dentin underneath becomes exposed. This can lead to tooth sensitivity, for example, with cold and hot food and drinks.

What does Sensodyne do?

Sensodyne provides daily care for sensitive teeth* plus all the benefits you would expect from a daily

fluoride toothpaste - strong teeth and freshness.
*with twice daily brushing.

24/7 SENSITIVITY PROTECTION* + Strong & Healthy Teeth

Use Sensodyne Fresh Mint twice daily:

• Long lasting sensitivity protection• every day

• Contains fluoride to protect against cavities

62000000208036 Front Carton

Principal Display Panel

NDC 0135-0528-04

#1 Dentist Recommended Brand

SENSODYNE

Fresh Impact

TOOTHPASTE FOR SENSITIVE TEETH AND CAVITY PREVENTION

24/7 SENSITIVITY PROTECTION* + Strong & Healthy Teeth

NET WT 4.0 OZ (113g)

What are sensitive teeth?

Lots of people have sensitive teeth. When enamel is worn away (through eating everyday acidic food or drinks) or gums recede, the dentin underneath becomes exposed. This can lead to tooth sensitivity, for example, with cold and hot food and drinks.

What does Sensodyne do?

Sensodyne provides daily care for sensitive teeth* plus all the benefits you would expect from a daily

fluoride toothpaste - strong teeth and freshness.
*with twice daily brushing

24/7 SENSITIVITY PROTECTION* +Strong & Healthy Teeth

Use Sensodyne Fresh Impact twice daily:

• Long lasting sensitivity protection• every day

• Contains fluoride to protect against cavities

6191 Front Carton